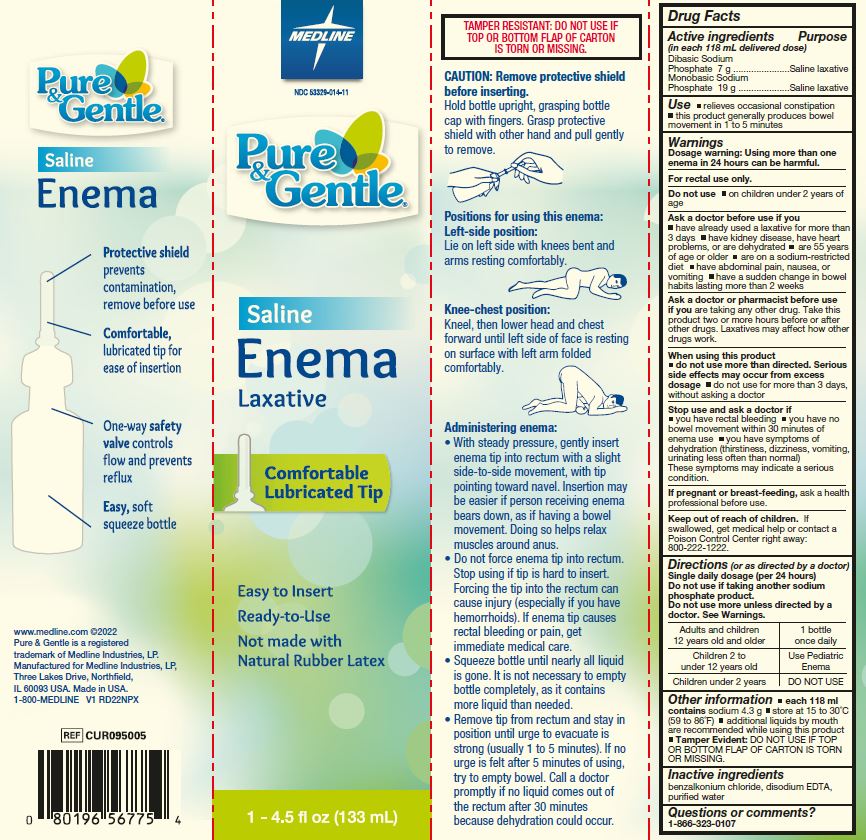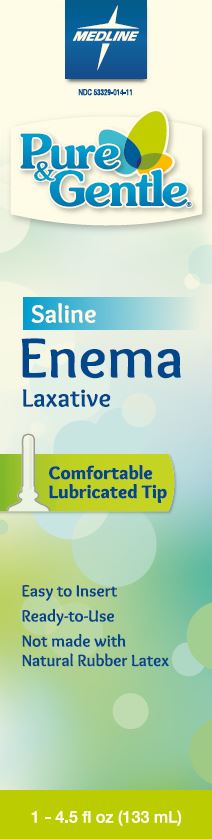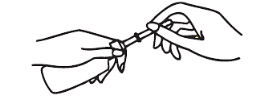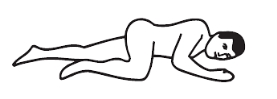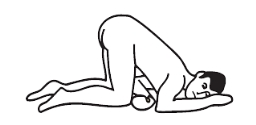 DRUG LABEL: Pure and Gentle Laxative
NDC: 53329-014 | Form: ENEMA
Manufacturer: Medline Industries, LP
Category: otc | Type: HUMAN OTC DRUG LABEL
Date: 20241126

ACTIVE INGREDIENTS: SODIUM PHOSPHATE, DIBASIC 7 g/118 mL; SODIUM PHOSPHATE, MONOBASIC 19 g/118 mL
INACTIVE INGREDIENTS: BENZALKONIUM CHLORIDE; EDETATE DISODIUM; WATER

014 Pure & Gentle Saline Enema Laxative

Active ingredient

(in each 118 mL delivered dose)

Dibasic sodium phosphate 7 g

Monobasic sodium phosphate 19 g

Purpose

Saline laxative

Uses

- relieves occasional constipation
- this product generally produces bowel movement in 1 to 5 minutes

Warnings

Dosage warning: Using more than one enema in 24 hours can be harmful.

For rectal use only.

Do not use

- on children under 2 years of age

Ask a doctor before use if you

- have already used a laxative for more than 3 days
- have kidney disease, have heart problems, or are dehydrated
- are 55 years of age or older
- are on a sodium-restricted diet
- have abdominal pain, nausea or vomiting
- have a sudden change in bowel habits lasting more than 2 weeks

Ask a doctor or pharmacist before use if you

are taking any other drug. Take this product two or more hours before or after other drugs. Laxatives may affect how other drugs work.

When using this product

- do not use more than directed. Serious side effects may occur from excess dosage
- do not use for more than 3 days, without asking a doctor

Stop use and ask a doctor if

- you have rectal bleeding
- you have no bowel movement within 30 minutes of enema use
- you have symtoms of dehydration (thirstiness, dissiness, vomiting, urinating less oftan than normal)

These symptoms may indicate a serious condition.

If pregnant or breastfeeding,

ask a health professional before use.

Keep out of reach of children.

If swallowed, get medical help or contact a Poison Control Center right away: 1-800-222-1222.

Directions

(or as directed by a doctor)

Single daily dosage (per 24 hours)

Do not use if taking another sodium phosphate product.

Do not use more unless directed by a doctor. See Warnings.

adults & children; 12 years and over | 1 bottle once daily
children 2 to under; 12 years | Use Pediatric Enema
children under; 2 years | DO NOT USE

CAUTION: Remove protective shield from enema tip before inserting.

Hold bottle upright, grasping bottle cap with fingers. Grasp protective shield with other hand and pull gently to remove.

Positions for using this enema:

Left-side position: lie on left side with knee bent and arms at rest.

Knee-chest position: kneel, then lower head and chest forward until left side of face is resting on surface with left arm folded comfortably.

Administering enema:

- With steady pressure, gently insert enema tip into rectum with a slight side to side movement, with tip pointing toward navel. Insertion may be easier if person receiving enema bears down, as if having a bowel movement. Doing so helps relax muscles around anus.
- Do not force enema tip into rectum. Stop using if tip is hard to insert. Forcing the tip into the rectum can cause injury (especially if you have hemorrhoids). If enema tip causes rectal bleeding or pain, get immediate medical care.
- Squeeze bottle until nearly all liquid is gone. It is not necessary to empty unit completely, as it containsmore liquid than needed.
- Remove tip from rectum and stay in position until urge to evacuate is strong (usually 1 to 5 minutes). If no urge is felt after 5 minutes of using, try to empty bowel. Call a doctor promptly if no liquid comes out of the rectum after 30 minutes because dehydration could occur.

Directions

(or as directed by a doctor)

Single daily dosage (per 24 hours)

Do not use if taking another sodium phosphate product.

Do not use more unless directed by a doctor. See Warnings

Adults and children 12 years old and older | 1 bottle once daily
Children 2 to under 12 years old | Use Pediatric Enema
Children under 2 years | DO NOT USE

CAUTION: Remove protective shield from enema tip before inserting.

Hold bottle upright, grasping bottle cap with fingers. Grasp protective shield with other hand and pull gently to remove.

Positions for using this enema:

Left-side position:
Lie on left side with knees bent and arms resting comfortably.

Knee-chest position:
Kneel, then lower head and chest forward until left side of face is resting on surface with left arm folded comfortably.

Administering enema:

- With steady pressure, gently insert enema tip into rectum with a slight side-to-side movement, with tip pointing toward navel. Insertion may be easier if person receiving enema bears down, as if having a bowel movement. Doing so helps relax muscles around anus.
- Do not force enema tip into rectum. Stop using if tip is hard to insert. Forcing the tip into the rectum can cause injury (especially if you have hemorrhoids). If enema tip causes rectal bleeding or pain, get immediate medical care.
- Squeeze bottle until nearly all liquid is gone. It is not necessary to empty bottle completely, as it contains more liquid than needed.
- Remove tip from rectum and stay in position until urge to evacuate is strong (usually 1 to 5 minutes). If no urge is felt after 5 minutes of using, try to empty bowel. Call a doctor promptly if no liquid comes out of the rectum after 30 minutes because dehydration could occur.

Other Information

- each 118 mL contains sodium 4.3 g
- store at15-30°C (59-86°F)
- additional liquids by mouth are recommended while using this product
- Tamper Evident: DO NOT USE IF TOP OR BOTTOM FLAP OF CARTON IS TORN OR MISSING

Inactive ingredients

benzalkonium chloride, disodium EDTA, purified water

Questions or comments?

866-323-0107

Manufacturing Information

Manufactured for:

Medline Industries, LP

Three Lakes Drive, Northfield, IL 60093 USA

Made in USA

www.medline.com

1-800-MEDLINE (633-5463)

REF: CUR095005

V1 RD22NPX